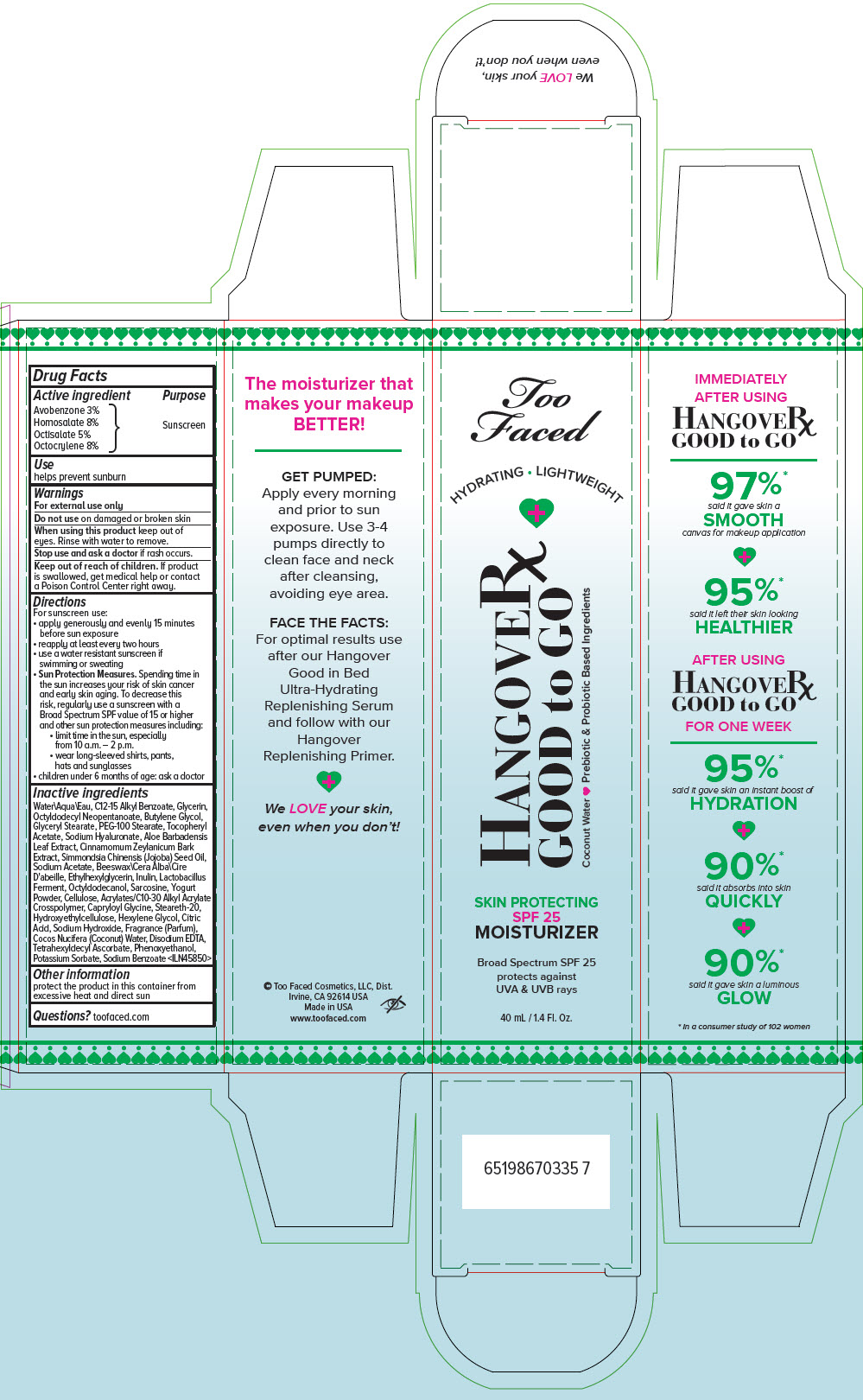 DRUG LABEL: TOO FACED HANGOVER GOOD TO GO SPF 25 BROAD SPECTRUM MOISTURIZER
NDC: 59735-991 | Form: LOTION
Manufacturer: MANA PRODUCTS, INC.
Category: otc | Type: HUMAN OTC DRUG LABEL
Date: 20240628

ACTIVE INGREDIENTS: AVOBENZONE 30 mg/1 mL; HOMOSALATE 80 mg/1 mL; OCTISALATE 50 mg/1 mL; OCTOCRYLENE 80 mg/1 mL
INACTIVE INGREDIENTS: ALKYL (C12-15) BENZOATE; WATER; GLYCERIN; OCTYLDODECYL NEOPENTANOATE; BUTYLENE GLYCOL; GLYCERYL MONOSTEARATE; PEG-100 STEARATE; .ALPHA.-TOCOPHEROL ACETATE; HYALURONATE SODIUM; ALOE VERA LEAF; CINNAMON BARK OIL; JOJOBA OIL; SODIUM ACETATE; ETHYLHEXYLGLYCERIN; INULIN; LIMOSILACTOBACILLUS REUTERI; OCTYLDODECANOL; SARCOSINE; POWDERED CELLULOSE; CARBOMER INTERPOLYMER TYPE A (ALLYL SUCROSE CROSSLINKED); CAPRYLOYL GLYCINE; STEARETH-20; HEXYLENE GLYCOL; CITRIC ACID MONOHYDRATE; SODIUM HYDROXIDE; COCONUT WATER; EDETATE DISODIUM ANHYDROUS; TETRAHEXYLDECYL ASCORBATE; PHENOXYETHANOL; POTASSIUM SORBATE; SODIUM BENZOATE

TOO FACED HANGOVER GOOD TO GO SPF 25 BROAD SPECTRUM MOISTURIZER

Drug Facts

Active ingredient

Avobenzone 3%
Homosalate 8%
Octisalate 5%
Octocrylene 8%

Purpose

Sunscreen

Use

helps prevent sunburn

Warnings

For external use only

Do not useon damaged or broken skin

WHEN USING

When using this productkeep out of eyes. Rinse with water to remove.

Stop use and ask a doctorif rash occurs.

Keep out of reach of children.If product is swallowed, get medical help or contact a Poison Control Center right away.

Directions

For sunscreen use:

- apply generously and evenly 15 minutes before sun exposure
- reapply at least every two hours
- use a water resistant sunscreen if swimming or sweating
- Sun Protection Measures.Spending time in the sun increases your risk of skin cancer and early skin aging. To decrease this risk, regularly use a sunscreen with a Broad Spectrum SPF value of 15 or higher and other sun protection measures including:
  - limit time in the sun, especially from 10 a.m. – 2 p.m.
  - wear long-sleeved shirts, pants, hats and sunglasses
- children under 6 months of age: ask a doctor

Inactive ingredients

Water\Aqua\Eau, C12-15 Alkyl Benzoate, Glycerin, Octyldodecyl Neopentanoate, Butylene Glycol, Glyceryl Stearate, PEG-100 Stearate, Tocopheryl Acetate, Sodium Hyaluronate, Aloe Barbadensis Leaf Extract, Cinnamomum Zeylanicum Bark Extract, Simmondsia Chinensis (Jojoba) Seed Oil, Sodium Acetate, Beeswax\Cera Alba\Cire D'abeille, Ethylhexylglycerin, Inulin, Lactobacillus Ferment, Octyldodecanol, Sarcosine, Yogurt Powder, Cellulose, Acrylates/C10-30 Alkyl Acrylate Crosspolymer, Capryloyl Glycine, Steareth-20, Hydroxyethylcellulose, Hexylene Glycol, Citric Acid, Sodium Hydroxide, Fragrance (Parfum), Cocos Nucifera (Coconut) Water, Disodium EDTA, Tetrahexyldecyl Ascorbate, Phenoxyethanol, Potassium Sorbate, Sodium Benzoate <ILN45850>

Other information

protect the product in this container from excessive heat and direct sun

Questions?

toofaced.com

PRINCIPAL DISPLAY PANEL - 40 mL Tube Carton

Too
Faced

HYDRATING • LIGHTWEIGHT

HANGOVERx
GOOD to GO

Coconut Water
Prebiotic & Probiotic Based Ingredients

SKIN PROTECTING
SPF 25
MOISTURIZER

Broad Spectrum SPF 25
protects against
UVA & UVB rays

40 mL / 1.4 Fl. Oz.